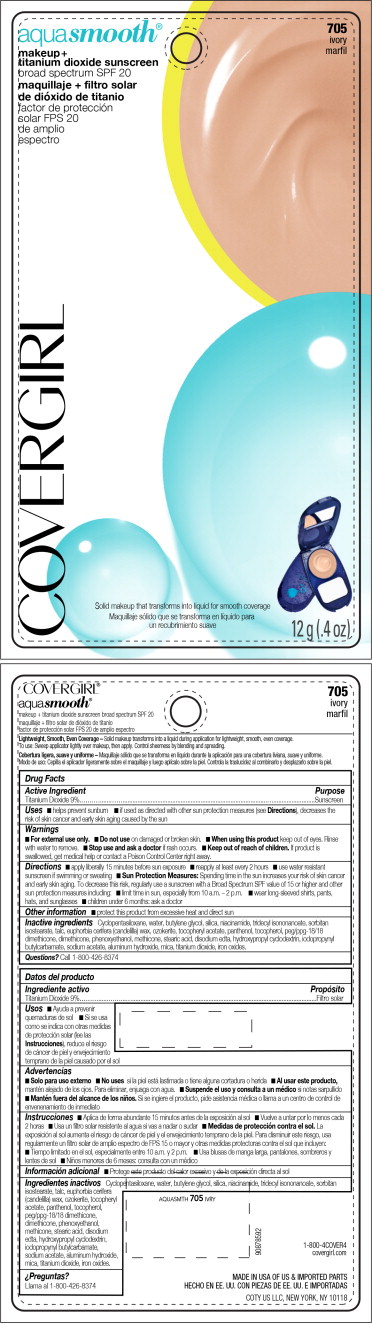 DRUG LABEL: Covergirl Aquasmooth
NDC: 22700-084 | Form: CREAM
Manufacturer: Noxell Corporation
Category: otc | Type: HUMAN OTC DRUG LABEL
Date: 20241120

ACTIVE INGREDIENTS: TITANIUM DIOXIDE 9 g/100 g
INACTIVE INGREDIENTS: TALC; CYCLOMETHICONE 5; WATER; BUTYLENE GLYCOL; SILICON DIOXIDE; NIACINAMIDE; SORBITAN ISOSTEARATE; CANDELILLA WAX; .ALPHA.-TOCOPHEROL ACETATE; PANTHENOL; TOCOPHEROL; PEG/PPG-18/18 DIMETHICONE; DIMETHICONE; PHENOXYETHANOL; STEARIC ACID; EDETATE DISODIUM; IODOPROPYNYL BUTYLCARBAMATE; SODIUM ACETATE; ALUMINUM HYDROXIDE; MICA; FERRIC OXIDE RED

Covergirl Aquasmooth®
Broadspectrum SPF 20 All shades

Drug Facts

Active Ingredient

Titanium Dioxide 9%

Purpose

Sunscreen

Uses

- helps prevent sunburn
- if used as directed with other sun protection measures (see Directions), decreases the risk of skin cancer and early skin aging caused by the sun

Warnings

- For external use only.

- Do not use on damaged or broken skin.

- When using this product keep out of eyes. Rinse with water to remove.

- Stop use and ask a doctor if rash occurs.

- Keep out of reach of children. If product is swallowed, get medical help or contact a Poison Control Center right away.

Directions

- apply liberally 15 minutes before sun exposure
- reapply at least every 2 hours
- use water resistant sunscreen if swimming or sweating
- Sun Protection Measures: Spending time in the sun increases your risk of skin cancer and early skin aging. To decrease this risk, regularly use a sunscreen with a Broad Spectrum SPF value of 15 or higher and other sun protection measures including:
  - limit time in sun, especially from 10 a.m. – 2 p.m.
  - wear long-sleeved shirts, pants, hats, and sunglasses
- children under 6 months: ask a doctor

Other information

- protect this product from excessive heat and direct sun

Inactive ingredients

Cyclopentasiloxane, water, butylene glycol, silica, niacinamide, tridecyl isononanoate, sorbitan isostearate, talc, euphorbia cerifera (candelilla) wax, ozokerite, tocopheryl acetate, panthenol, tocopherol, peg/ppg-18/18 dimethicone, dimethicone, phenoxyethanol, methicone, stearic acid, disodium edta, hydroxypropyl cyclodextrin, iodopropynyl butylcarbamate, sodium acetate, aluminum hydroxide, mica, titanium dioxide, iron oxides.

Questions?

Call 1-800-426-8374

PRINCIPAL DISPLAY PANEL - 12 g Case Blister Pack

aqua smooth®

makeup+
titanium dioxide sunscreen
broad spectrum SPF 20

705
ivory

COVERGIRL

Solid makeup that transforms into liquid for smooth coverage

12 g (.4 oz)